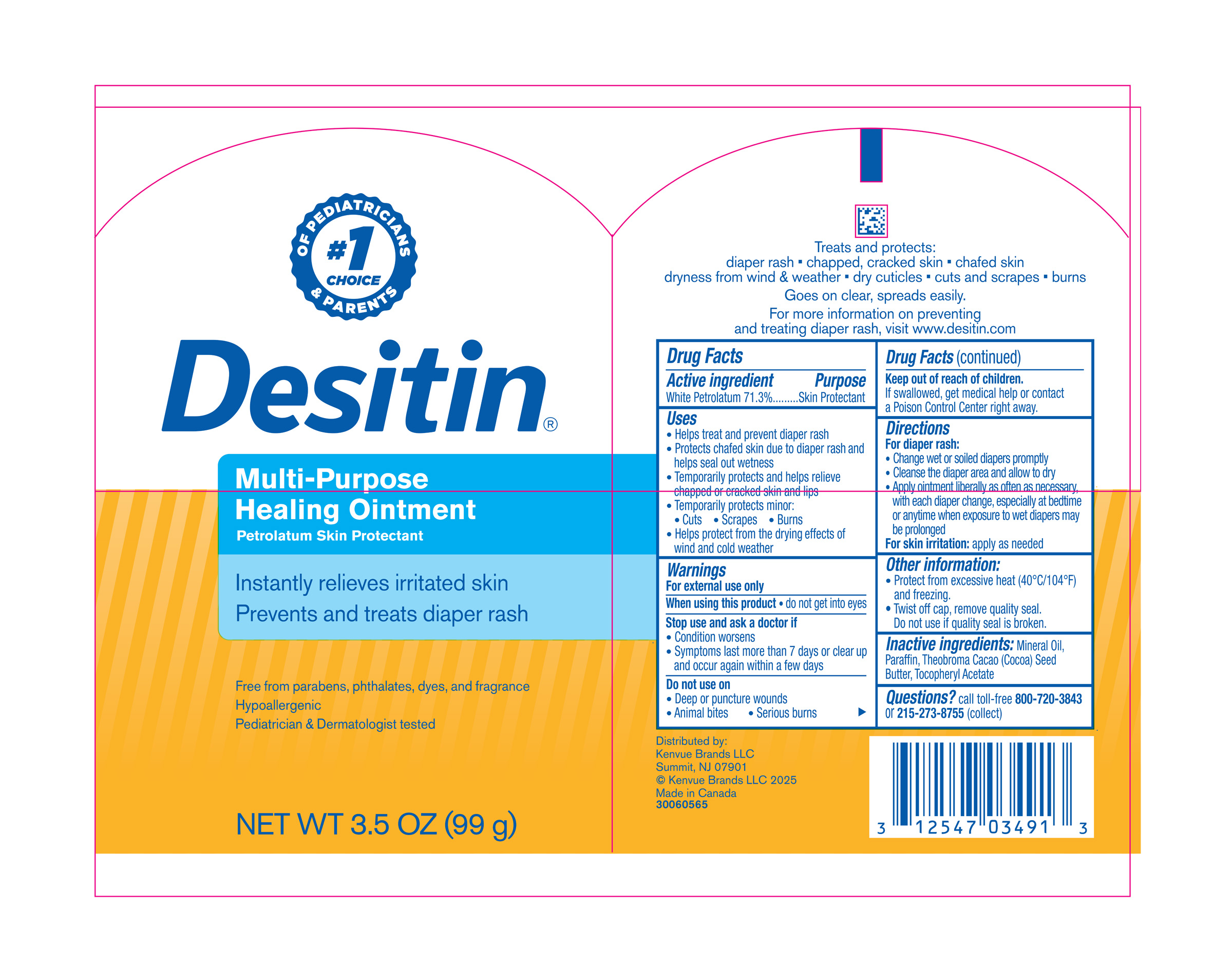 DRUG LABEL: Desitin Multi-Purpose Healing
NDC: 69968-0494 | Form: OINTMENT
Manufacturer: Kenvue Brands LLC
Category: otc | Type: HUMAN OTC DRUG LABEL
Date: 20250707

ACTIVE INGREDIENTS: PETROLATUM 713 mg/1 g
INACTIVE INGREDIENTS: MINERAL OIL; PARAFFIN; COCOA BUTTER; .ALPHA.-TOCOPHEROL ACETATE

Desitin® Multi-Purpose Healing Ointment

Drug Facts

Active ingredient

White Petrolatum 71.3%

Purpose

Skin Protectant

Uses

- Helps treat and prevent diaper rash
- Protects chafed skin due to diaper rash and helps seal out wetness
- Temporarily protects and helps relieve chapped or cracked skin and lips
- Temporarily protects minor:
  - Cuts
  - Scrapes
  - Burns
- Helps protect from the drying effects of wind and cold weather

Warnings

For external use only

When using this product

- do not get into eyes

Stop use and ask a doctor if

- Condition worsens
- Symptoms last more than 7 days or clear up and occur again within a few days

Do not use on

- Deep or puncture wounds
- Animal bites
- Serious burns

Keep out of reach of children. If swallowed, get medical help or contact a Poison Control Center right away.

Directions

For diaper rash:

- Change wet or soiled diapers promptly
- Cleanse the diaper area and allow to dry
- Apply ointment liberally as often as necessary, with each diaper change, especially at bedtime or anytime when exposure to wet diapers may be prolonged

For skin irritation: apply as needed

Other Information

- Protect from excessive Heat (40°C/104°F) and freezing.
- Twist off cap, remove quality seal. Do not use if quality seal is broken.

Inactive ingredients

Mineral Oil, Paraffin, Theobroma Cacao (Cocoa) Seed Butter, Tocopheryl Acetate

Questions?

Call toll-free 800-720-3843 or 215-273-8755 (collect)

Distributed by:
Kenvue Brands LLC
Summit, NJ 07901

PRINCIPAL DISPLAY PANEL - 99 g Jar Label

OF PEDIATRICIANS
#1
CHOICE
& PARENTS
Desitin®
Multi-Purpose

Healing Ointment
Petrolatum skin protectant
Instantly relieves irritated skin
Prevents and treats diaper rash

Free from parabens, phthalates, dyes, and fragrance
Hypoallergenic

Pediatrician & Dermatologist tested
NET WT 3.5 OZ (99 g)